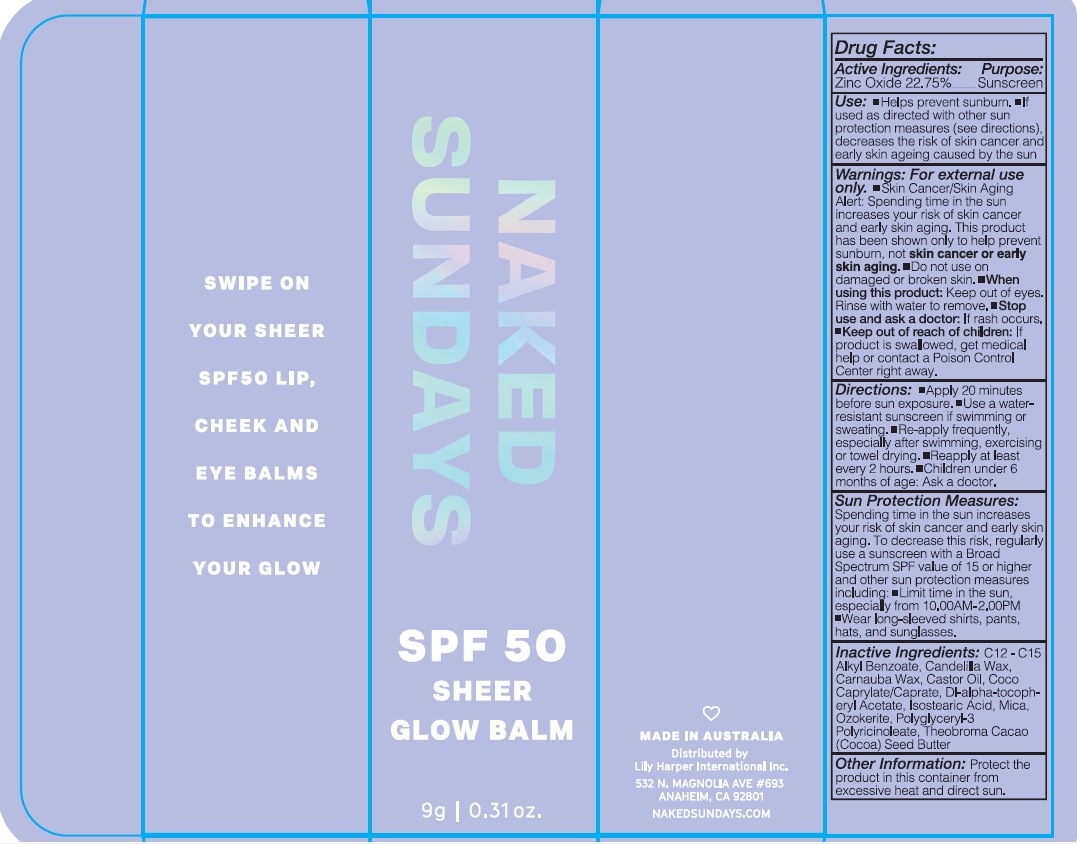 DRUG LABEL: SPF50 SHEER GLOW BALM ESPRESSO MARTINI 9g
NDC: 81104-897 | Form: LIPSTICK
Manufacturer: NAKED SUNDAY PTY LTD
Category: otc | Type: HUMAN OTC DRUG LABEL
Date: 20250322

ACTIVE INGREDIENTS: ZINC OXIDE 22.75 g/100 g
INACTIVE INGREDIENTS: CARNAUBA WAX; ISOSTEARIC ACID; CERESIN; COCO-CAPRYLATE/CAPRATE; C12-20 ALKYL BENZOATE; CANDELILLA WAX; CASTOR OIL; MICA; THEOBROMA GRANDIFLORUM SEED BUTTER; POLYGLYCERYL-3 PENTARICINOLEATE; .ALPHA.-TOCOPHEROL ACETATE, D-

NAKED SUNDAYS SPF50 SHEER GLOW BALM ESPRESSO MARTINI 9g

ACTIVE INGREDIENTS

ZINC OXIDE 22.75 %

PURPOSE

SUNSCREEN

USE

- Helps prevents sunburn

- If used as directed with other sun protection measures (see directions) decreases the risk of skin cancer and early skin ageing caused by the sun.

WARNINGS

FOR EXTERNAL USE ONLY

- Do not use on damaged or broken skin.

Skin Cancer/Skin Aging Alert: Spending time in the sun
increases your risk of skin cancer and early skin aging.
To decrease this risk, regularly use a sunscreen with broad spectrum SPF value of 15 or higher and other sun protection measure including - Limit time in the sun especially from 10:00 AM to 2: 00 PM , Wear Long Slleve Shirts, pants hats and Sunglasses.

WHEN USING

keep out of eyes, Rinse with water to remove

Stop use & ask doctor

If rash occurs

KEEP OUT OF REACH OF CHILDREN

If product is swallowed , get medical help or contact a poison control center right away

Directions

Apply generously 20 minutes before sun exposure.
Use a water-resistant sunscreen if swimming or sweating.
Reapply immediately after towel drying.
Reapply at least every 2 hours.
Children under 6 months of age: Ask a doctor.

Sun Protection Measures :

Spending time in the sun increases your risk of skin cancer and early skin aging. To decrease this risk, regularly use a sunscreen with a Broad spectrum SPF value of 15 or higher and other sun protection measures inclusing:

- limit time in the sun, especially from 10:00 AM- 02:00 PM

- Wear long- Sleeved shirts , pants, Hats and sunglasses

Inactive Ingredients

C12- C15 Alkyl Benzoate, Candelilla Wax, Carnauba Wax, Castor Oil. Coco Caprylate/Caprate, Dl-alpha-tocopheryl Acetate, Isostearic Acid, Mica, Ozokerite, Polyglyceryl-3 Polyglyceryl-3 Polyricinoleate, Theobroma Cacao (Cocoa) Seed Butter

OTHER SAFETY INFORMATION

Protect the product in this container from excessive heat & direct sun

DOSAGE AND ADMINISTRATION

for external use only